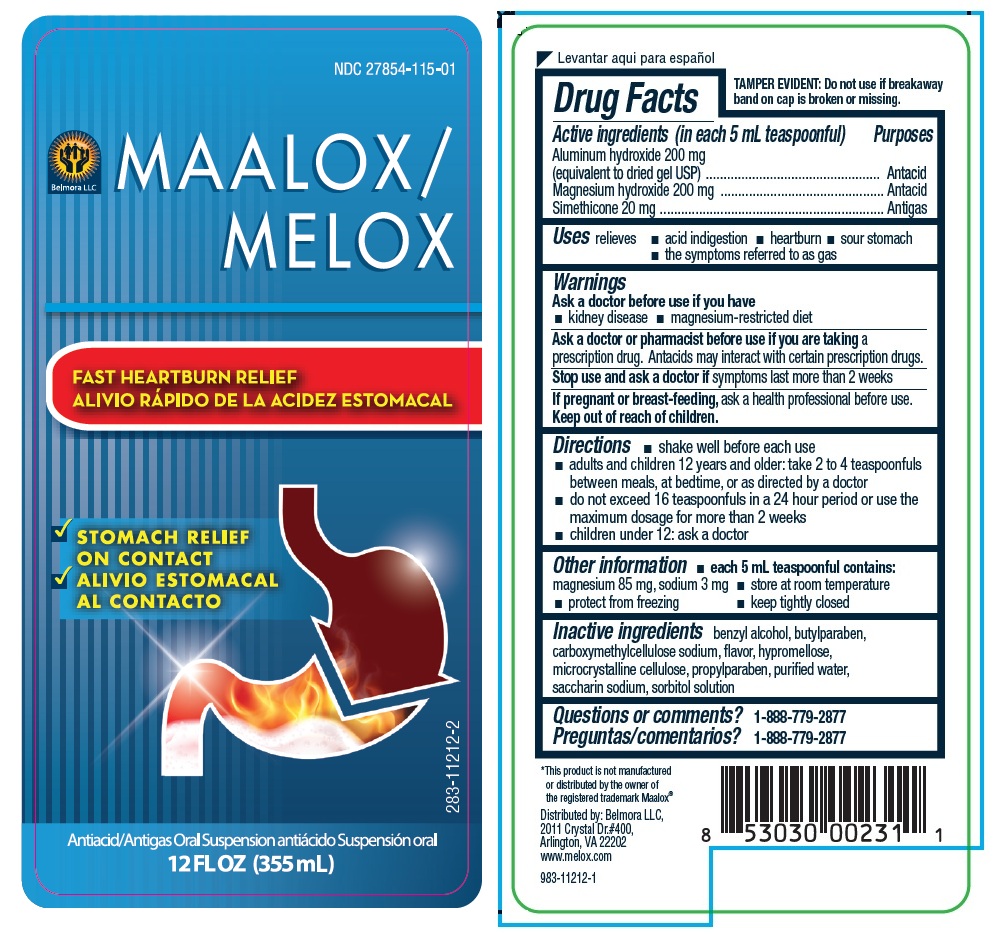 DRUG LABEL: Melox
NDC: 27854-115 | Form: SUSPENSION
Manufacturer: Belmora LLC
Category: otc | Type: HUMAN OTC DRUG LABEL
Date: 20251120

ACTIVE INGREDIENTS: ALUMINUM HYDROXIDE 200 mg/5 mL; MAGNESIUM HYDROXIDE 200 mg/5 mL; DIMETHICONE, UNSPECIFIED 20 mg/5 mL
INACTIVE INGREDIENTS: BENZYL ALCOHOL; BUTYLPARABEN; CARBOXYMETHYLCELLULOSE SODIUM, UNSPECIFIED; HYPROMELLOSE, UNSPECIFIED; MICROCRYSTALLINE CELLULOSE; PROPYLPARABEN; WATER; SACCHARIN SODIUM; SORBITOL SOLUTION

Melox

Active ingredients (in each 5 mL teaspoonful)

Aluminum hydroxide 200 mg (equivalent to dried gel USP)

Magnesium hydroxide 200 mg

Simethicone 20 mg

Purpose

Antacid

Antacid

Antigas

Uses

relieves • acid indigestion • heartburn • sour stomach • the symptoms referred to as gas

Warnings

Ask a doctor before use if you have

• kidney disease • magnesium-restricted diet

Ask a doctor or pharmacist before use if you are taking a prescription drug. Antacids may interact with certain prescription drugs.

Stop use and ask a doctor if symptoms last more than 2 weeks

If pregnant or breast-feeding, ask a health professional before use.

Keep out of reach of children.

Directions

• shake well before each use

• adults and children 12 years and older: take 2 to 4 teaspoonfuls between meals, at bedtime, or as directed by a doctor

• do not exceed 16 teaspoonfuls in a 24 hour period or use the maximum dosage for more than 2 weeks

• children under 12: ask a doctor

Other information

• each 5 mL teaspoonful contains: magnesium 85 mg, sodium 3 mg

• store at room temperature

• protect from freezing

• keep tightly closed

Inactive ingredients

benzyl alcohol, butylparaben, carboxymethylcellulose sodium, flavor, hypromellose, microcrystalline cellulose, propylparaben, purified water, saccharin sodium, sorbitol solution

Questions or comments?

1-888-779-2877

FAST HEARTBURN RELIEF

STOMACH RELIEF ON CONTACT

TAMPER EVIDENT: Do not use if breakaway band on cap is broken or missing.

*This product is not manufactured or distributed by the owner of the registered trademark Maalox®

Distributed by: Belmora LLC,
2011 Crystal Dr.#400,
Arlington, VA 22202
www.melox.com